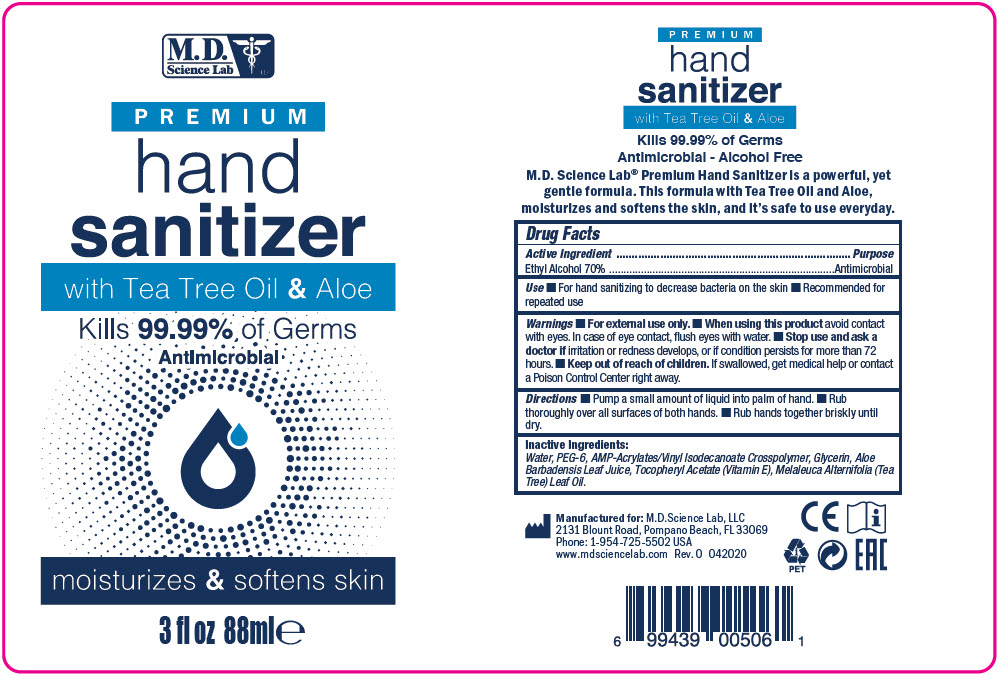 DRUG LABEL: PREMIUM HAND SANITIZER
NDC: 69898-601 | Form: LIQUID
Manufacturer: MD Science Lab LLC
Category: otc | Type: HUMAN OTC DRUG LABEL
Date: 20200414

ACTIVE INGREDIENTS: Alcohol 70 mL/100 mL
INACTIVE INGREDIENTS: Water; Glycerin; POLYETHYLENE GLYCOL 300; Aloe Vera Leaf; TEA TREE OIL

PREMIUM HAND SANITIZER

Drug Facts

Active Ingredient

Ethyl Alcohol 70%

Purpose

Antimicrobial

Use

- For hand sanitizing to decrease bacteria on the skin
- Recommended for repeated use

Warnings

- For external use only.

- When using this product avoid contact with eyes. In case of eye contact, flush eyes with water.

- Stop use and ask a doctor if irritation or redness develops, or if condition persists for more than 72 hours.

- Keep out of reach of children. If swallowed, get medical help or contact a Poison Control Center right away.

Directions

- Pump a small amount of liquid into palm of hand.
- Rub thoroughly over all surfaces of both hands.
- Rub hands together briskly until dry.

Inactive Ingredients

Water, PEG-6, AMP-Acrylates/Vinyl Isodecanoate Crosspolymer, Glycerin, Aloe Barbadensis Leaf Juice, Tocopheryl Acetate (Vitamin E), Melaleuca Alternifolia (Tea Tree) Leaf Oil.

PRINCIPAL DISPLAY PANEL - 88 ml Bottle Label

M.D.
Science Lab
LLC

PREMIUM
hand
sanitizer
with Tea Tree Oil & Aloe

Kills 99.99% of Germs
Antimicrobial

moisturizes & softens skin

3 fl oz 88ml℮